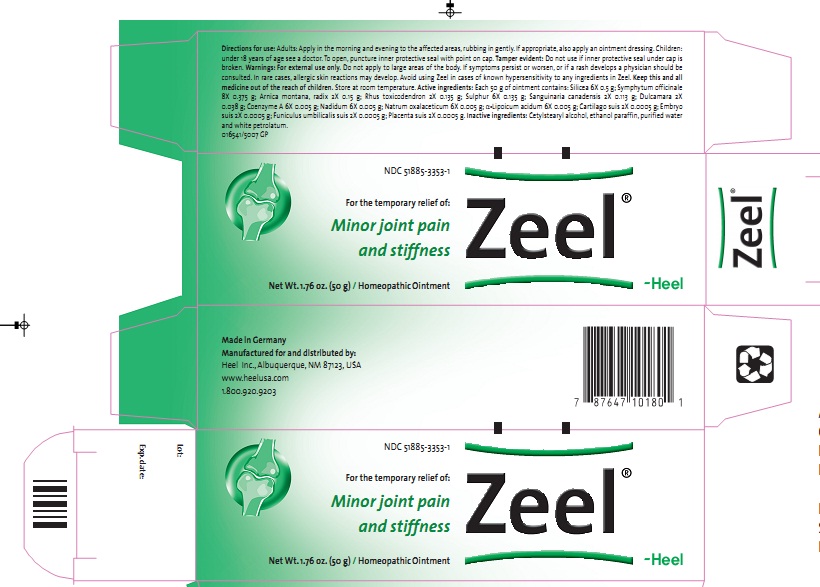 DRUG LABEL: Zeel
NDC: 51885-3353 | Form: OINTMENT
Manufacturer: Biologische Heilmittel Heel
Category: homeopathic | Type: HUMAN OTC DRUG LABEL
Date: 20120228

ACTIVE INGREDIENTS: SILICON DIOXIDE 6 [hp_X]/50 g; COMFREY ROOT  8 [hp_X]/50 g; ARNICA MONTANA ROOT 2 [hp_X]/50 g; TOXICODENDRON PUBESCENS LEAF  2 [hp_X]/50 g; SULFUR 6 [hp_X]/50 g; SANGUINARIA CANADENSIS ROOT 2 [hp_X]/50 g; SOLANUM DULCAMARA STEM  2 [hp_X]/50 g; COENZYME A  6 [hp_X]/50 g; NADIDE 6 [hp_X]/50 g; SODIUM DIETHYL OXALACETATE  6 [hp_X]/50 g; .ALPHA.-LIPOIC ACID 6 [hp_X]/50 g; SUS SCROFA CARTILAGE  2 [hp_X]/50 g; SUS SCROFA EMBRYO 2 [hp_X]/50 g; SUS SCROFA UMBILICAL CORD  2 [hp_X]/50 g; SUS SCROFA PLACENTA  2 [hp_X]/50 g
INACTIVE INGREDIENTS: CETOSTEARYL ALCOHOL; ALCOHOL ; WATER; PETROLATUM  ; PARAFFIN 

ACTIVE INGREDIENTS

Active ingredients: Each 50g of ointment contains: Silicea 6X 0.5g; Symphytum officinale 8X 0.375g; Arnica montana, radix 2X 0.15g; Rhus toxicodendron 2X 0.135g; Sulphur 6X 0.135g; Sanguinaria canadensis 2X 0.113g; Dulcamara 2X 0.038g; Coenzyme A 6X 0.005g; Nadidum 6X 0.005g; Natrum oxalaceticum 6X 0.005g; α- Lipoicum acidum 6X 0.005g; Cartilago suis 2X 0.0005g; Embryo suis 2X 0.0005g; Funiculus umbilicalis suis 2X 0.0005g; Placenta suis 2X 0.0005g.

PURPOSE

Minor joint pain and stiffness

KEEP OUT OF REACH OF CHILDREN

Keep this and all medicine out of the reach of children.

INDICATIONS AND USAGE

For the temporary relief of:

- Minor joint pain and stiffness

WARNINGS

Warnings: For external use only. Do not apply to large areas of the body. If symptoms persist or worsen, or if a rash develops a physician should be consulted. In rare cases, allergic skin reactions may develop. Avoid using Zeel in cases of known hypersensitivity to any ingredients in Zeel.

DOSAGE AND ADMINISTRATION

Direction for use: Adults: Apply in the morning and evening to the effected areas, rubbing in gently. If appropriate, also apply an ointment dressing. Children under 18 years of age see a doctor.

INACTIVE INGREDIENTS

Inactive ingredients: Cetylstearyl alcohol, ethanol, paraffin, purified water and white petrolatum.

PACKAGE LABEL

Zeel 50g Carton.jpg